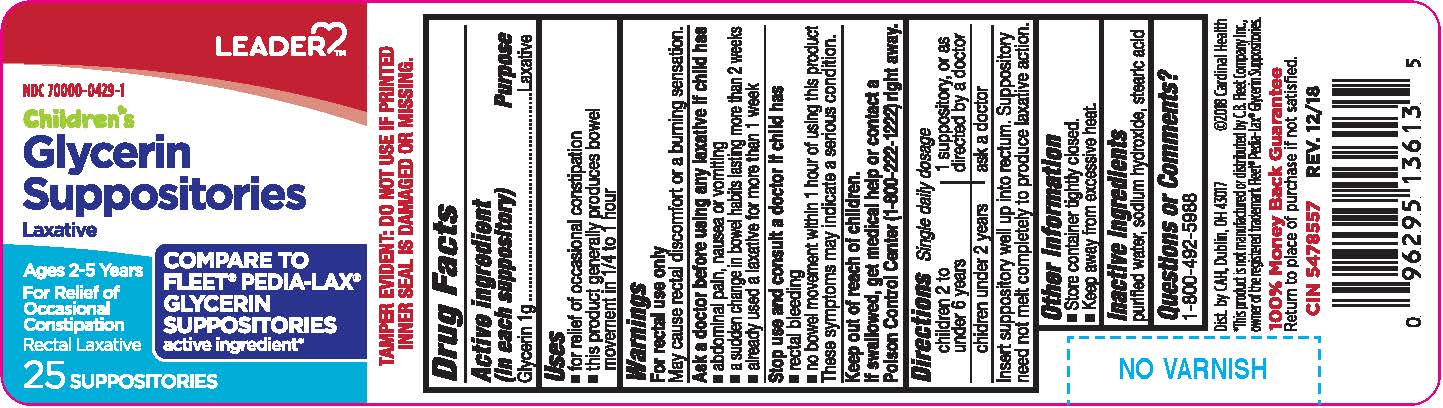 DRUG LABEL: Glycerin
NDC: 70000-0429 | Form: SUPPOSITORY
Manufacturer: Cardinal Health
Category: otc | Type: HUMAN OTC DRUG LABEL
Date: 20251024

ACTIVE INGREDIENTS: GLYCERIN 1 g/1 1
INACTIVE INGREDIENTS: SODIUM HYDROXIDE; STEARIC ACID; WATER

Leader Children's Glycerin Suppository

Active ingredient (in each suppository)

Glycerin 1g

Purpose

Laxative

Uses

- for relief of occassional constipation
- this product generally produces bowel movement in 1/4 to 1 hour

Warnings

For rectal use only

May cause rectal discomfort or a burning sensation.

Ask a doctor before using any laxative if child has

- abdominal pain, nausea or vomiting
- a sudden change in bowel habits lasting more than 2 weeks
- already used a laxative formore than 1 week

Stop use and consult a doctor if child has

- rectal bleeding
- no bowel movement within 1 hour using this product

These symptoms may indicate a serious condition.

Directions - single daily dose

children 2 to under 6 years - 1 suppository, or as directed by a doctor

chidren under 2 - ask a doctor

Insert suppository well up into rectum. Suppository need not melt completely to produce laxative action.

Other information

- Store container tightly closed.
- Keep away from excessive heat.

Inactive ingredients

purified water, sodium hydroxide, stearic acid

Questions or comments?

1-800-492-5988

Label

The product package shown below represents a sample of that currently in use. Additional packaging may also be available.

Children's Glycerin Suppositories, 25 count

Distributed by Cardinal Health, Dublin OH 43017

CH ChildSupp.jpg